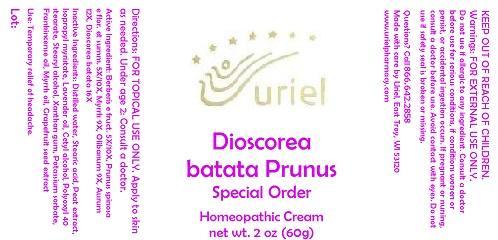 DRUG LABEL: Dioscorea batata Prunus Special Order
NDC: 48951-4112 | Form: CREAM
Manufacturer: Uriel Pharmacy Inc.
Category: homeopathic | Type: HUMAN OTC DRUG LABEL
Date: 20141002

ACTIVE INGREDIENTS: BERBERIS VULGARIS ROOT BARK 5 [hp_X]/1 g; SLOE 5 [hp_X]/1 g; MYRRH 9 [hp_X]/1 g; FRANKINCENSE 9 [hp_X]/1 g; GOLD 12 [hp_X]/1 g; CHINESE YAM 16 [hp_X]/1 g
INACTIVE INGREDIENTS: WATER; STEARIC ACID; SPHAGNUM SQUARROSUM PEAT; ISOPROPYL MYRISTATE; LAVENDER OIL; CETYL ALCOHOL; POLYOXYL 40 STEARATE; STEARYL ALCOHOL; XANTHAN GUM; POTASSIUM SORBATE; CITRUS PARADISI SEED; MYRRH OIL; FRANKINCENSE OIL

Dioscorea batata Prunus Special Order

INDICATIONS AND USAGE

Directions: FOR TOPICAL USE ONLY.

DOSAGE AND ADMINISTRATION

Apply to skin as needed. Under age 2: Consult a doctor.

Active Ingredient: Berberis e fruct. 5X/10X, Prunus spinosa e flor. et summ. 5X/10X, Myrrh 9X, Olibanum 9X, Aurum 12X, Dioscorea batata 16X

INACTIVE INGREDIENT

Inactive Ingredients: Distilled water, Stearic acid, Peat extract, Isopropyl myristate, Lavender oil, Cetyl alcohol, Polyoxyl 40 stearate, Stearyl alcohol, Xanthan gum, Potassium sorbate, Frankincense oil, Myrrh oil, Grapefruit seed extract

PURPOSE

Use: Temporary relief of headache.

KEEP OUT OF REACH OF CHILDREN.

WARNINGS

Warnings: FOR EXTERNAL USE ONLY. Do not use if allergic to any ingredient. Consult a doctor before use for serious conditions, if conditions worsen or persist, or accidental ingestion occurs. If pregnant or nursing, consult a doctor before use. Avoid contact with eyes. Do not use if safety seal is broken or missing.

QUESTIONS

Questions? Call 866.642.2858 Made with care by Uriel, East Troy, WI 53120 www.urielpharmacy.com